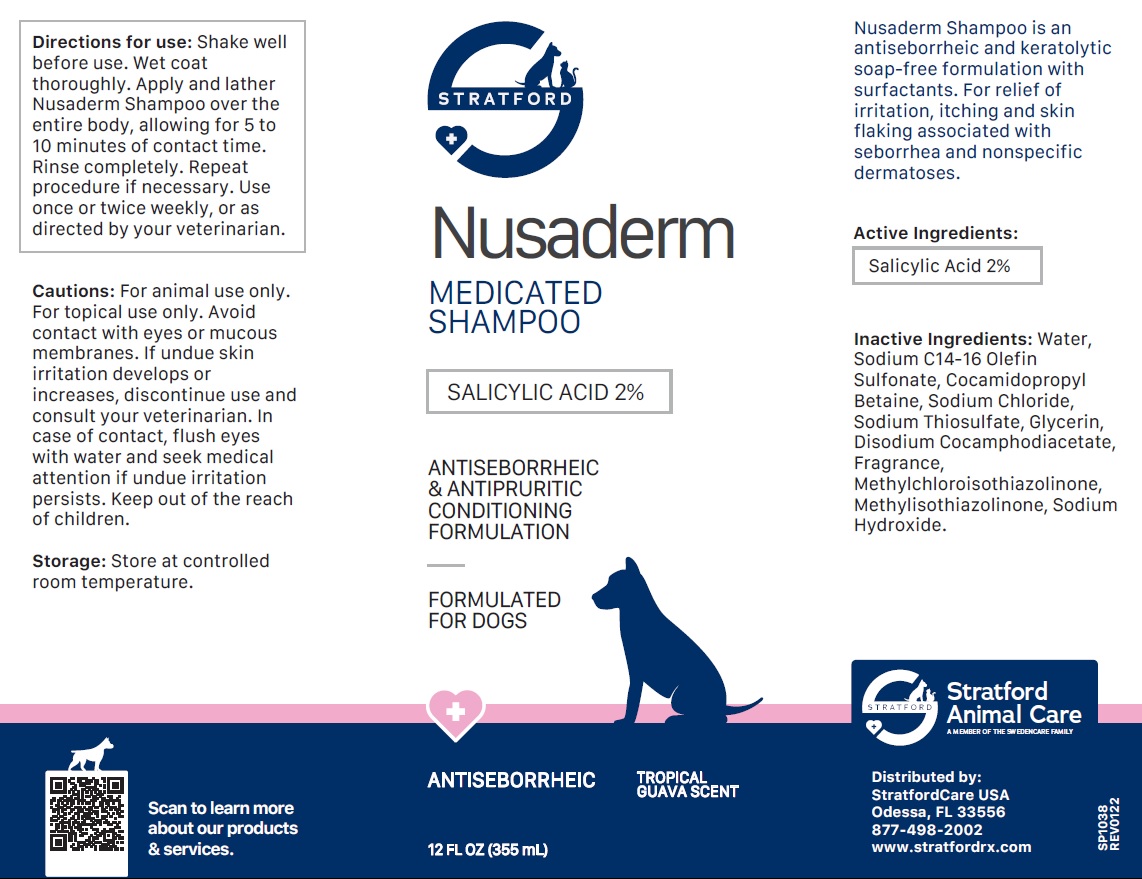 DRUG LABEL: Nusaderm MEDICATED
NDC: 86069-122 | Form: SHAMPOO
Manufacturer: Stratford Care Usa, Inc.
Category: animal | Type: OTC ANIMAL DRUG LABEL
Date: 20221121

ACTIVE INGREDIENTS: SALICYLIC ACID 2 g/100 mL
INACTIVE INGREDIENTS: WATER; SODIUM C14-16 OLEFIN SULFONATE; COCAMIDOPROPYL BETAINE; SODIUM CHLORIDE; SODIUM THIOSULFATE; GLYCERIN; DISODIUM COCOAMPHODIACETATE; METHYLCHLOROISOTHIAZOLINONE; METHYLISOTHIAZOLINONE; SODIUM HYDROXIDE

Nusaderm MEDICATED SHAMPOO

Active Ingredients:

Salicylic Acid 2%

PURPOSE

ANTISEBORRHEIC & ANTIPRURITIC

INDICATIONS AND USAGE

Nusaderm Shampoo is an antiseborrheic and keratolytic soap-free formulation with surfactants. For relief of irritation, itching and skin flaking associated with seborrhea and nonspecific dermatoses.

INACTIVE INGREDIENT

Inactive Ingredients: Water, Sodium C14-16 Olefin Sulfonate, Cocamidopropyl Betaine, Sodium Chloride, Sodium Thiosulfate, Glycerin, Disodium Cocoamphodiacetate, Fragrance, Methylchloroisothiazolinone, Methylisothiazolinone, Sodium Hydroxide.

DOSAGE AND ADMINISTRATION

Directions for use: Shake well before use. Wet coat thoroughly. Apply and lather Nusaderm Shampoo over the entire body, allowing for 5 to 10 minutes of contact time. Rinse completely. Repeat procedure if necessary. Use once or twice weekly, or as directed by your veterinarian.

PRECAUTIONS

Cautions: For animal use only. For topical use only. Avoid contact with eyes or mucous membranes. If undue skin irritation develops or increases, discontinue use and consult your veterinarian. In case of contact, flush eyes with water and seek medical attention if undue irritation persists. Keep out of the reach of children.

Storage: Store at controlled room temperature.

ANTISEBORRHEIC & ANTIPRURITIC CONDITIONING FORMULATION

FORMULATED FOR DOGS

TROPICAL GUAVA SCENT

Stratford Animal Care
A MEMBER OF THE SWEDENCARE FAMILY

Distributed by:
StratfordCare USA
Odessa, FL 33556
877-498-2002
www.stratfordrx.com